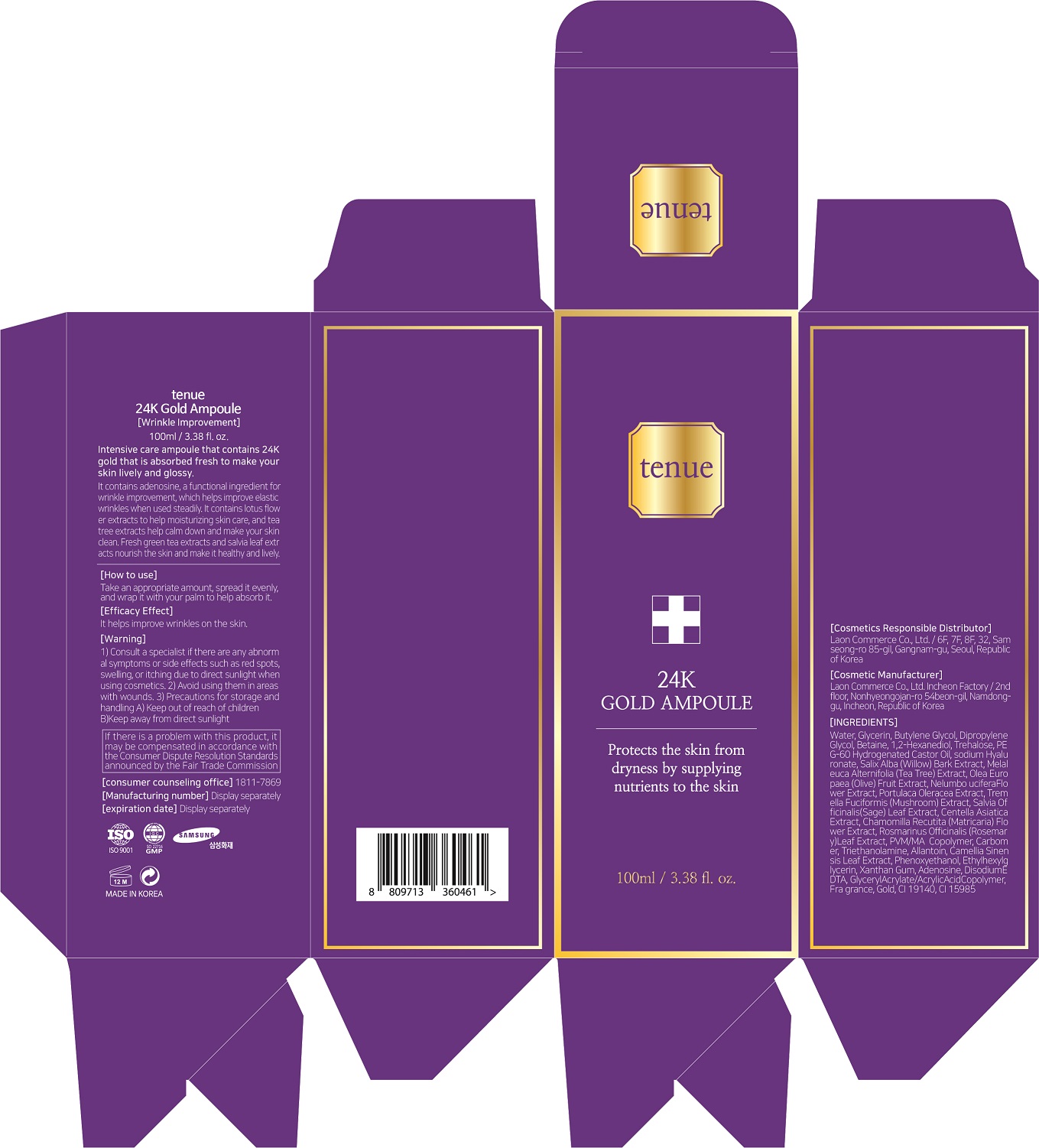 DRUG LABEL: Tenue 24k gold ampoule
NDC: 82083-0012 | Form: LIQUID
Manufacturer: LAON COMMERCE co ltd
Category: otc | Type: HUMAN OTC DRUG LABEL
Date: 20220918

ACTIVE INGREDIENTS: ADENOSINE 0.04 g/100 mL
INACTIVE INGREDIENTS: WATER

ACTIVE INGREDIENT

Adenosine

INACTIVE INGREDIENT

Water
Glycerin
Butylene Glycol
Dipropylene Glycol
Betaine
1,2-Hexanediol
Trehalose
PEG-60 Hydrogenated Castor Oil
Sodium Hyaluronate
Salix Alba (Willow) Bark Extract
Melaleuca Alternifolia (Tea Tree) Extract
Olea Europaea (Olive) Fruit Extract
Nelumbo Nucifera Flower Extract
Portulaca Oleracea Extract
Tremella Fuciformis (Mushroom) Extract
Salvia Officinalis (Sage) Leaf Extract
Centella Asiatica Extract
Chamomilla Recutita (Matricaria) Flower Extract
Rosmarinus Officinalis (Rosemary) Leaf Extract
PVM/MA Copolymer
Carbomer
Triethanolamine
Allantoin
Camellia Sinensis Leaf Extract
Phenoxyethanol
Ethylhexylglycerin
Xanthan Gum
Disodium EDTA
Glyceryl Acrylate/Acrylic Acid Copolymer
Fragrance
Gold
CI 19140
CI 15985

PURPOSE

It helps to improve wrinkles on the skin.

KEEP OUT OF REACH OF THE CHILDREN

INDICATIONS AND USAGE

taek an appropriate amount, spread it evenly, and wrap it with your palm to help absorb it

WARNINGS

1. consult a specialist if there are any abnormal symptoms or side effects such as red spots, swelling, or itching due to direct sunlight when using cosmetics

2. avoid using them in areas with wounds

3. precautions for storage and handling

a) keep out of reach of childrea

b) keep away from direct sunlight

DOSAGE AND ADMINISTRATION

topical use only